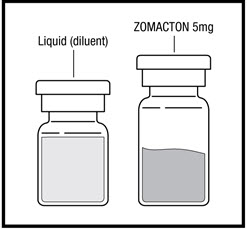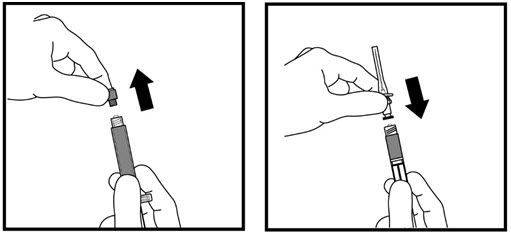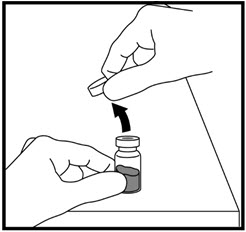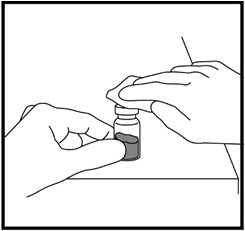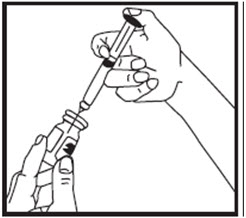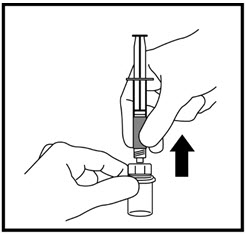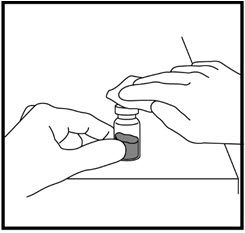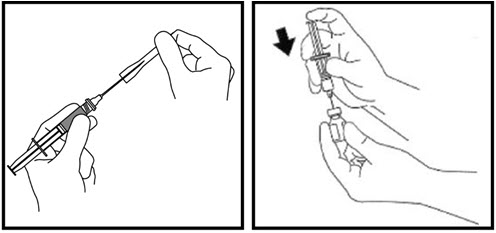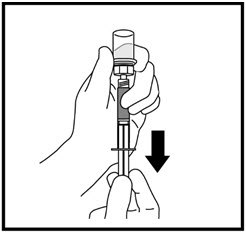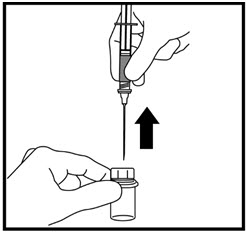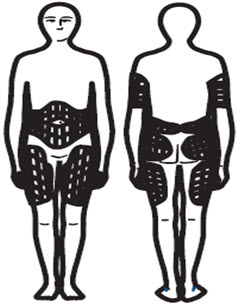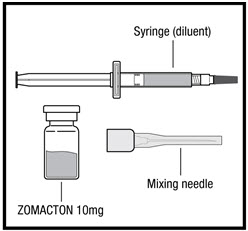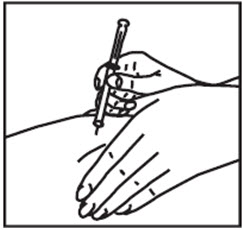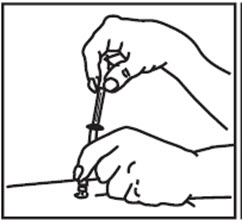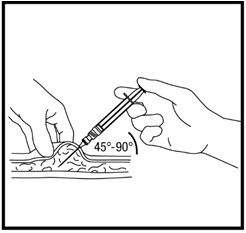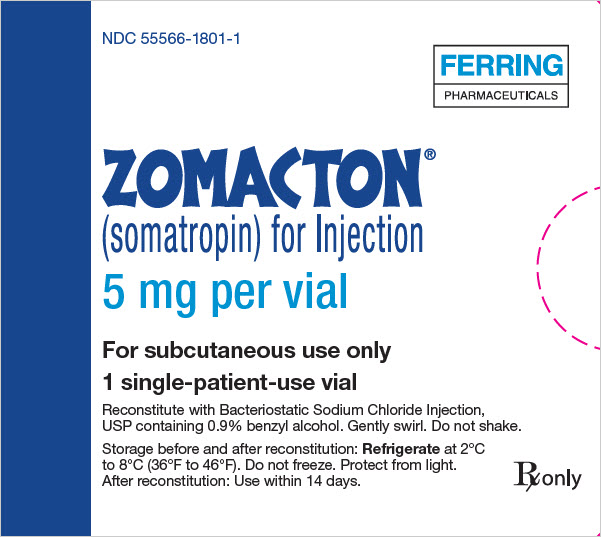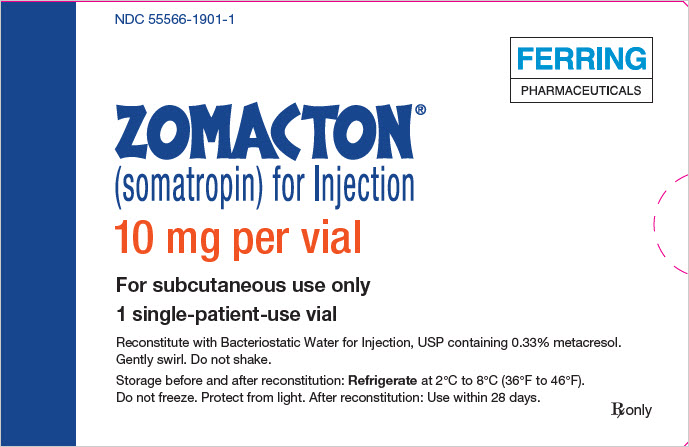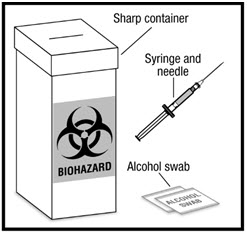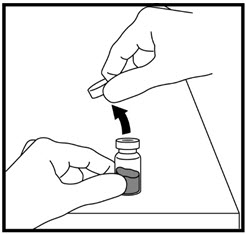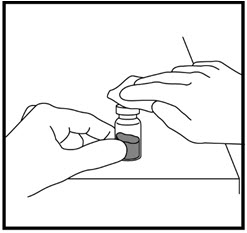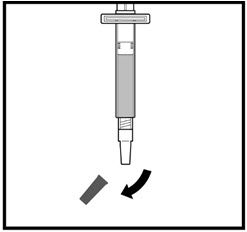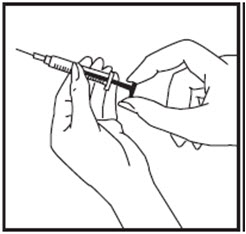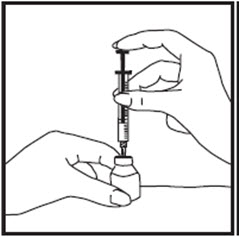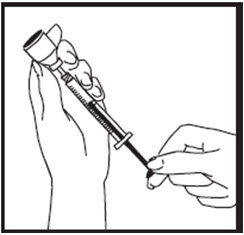 DRUG LABEL: ZOMACTON
NDC: 55566-1801 | Form: KIT | Route: SUBCUTANEOUS
Manufacturer: Ferring Pharmaceuticals Inc.
Category: prescription | Type: HUMAN PRESCRIPTION DRUG LABEL
Date: 20260224

ACTIVE INGREDIENTS: SOMATROPIN 5 mg/1 1
INACTIVE INGREDIENTS: MANNITOL 30 mg/1 1; WATER; BENZYL ALCOHOL; SODIUM CHLORIDE

HIGHLIGHTS OF PRESCRIBING INFORMATION

These highlights do not include all the information needed to use ZOMACTON® safely and effectively. See full prescribing information for ZOMACTON.
ZOMACTON® (somatropin) for injection, for subcutaneous use
Initial U.S. Approval: 1995

RECENT MAJOR CHANGES

Warning and Precautions, Slipped Capital Femoral Epiphysis in Pediatric Patients (5.10) 07/2025

1 INDICATIONS AND USAGE

ZOMACTON is a recombinant human growth hormone indicated for:

- Pediatric: Treatment of pediatric patients with growth failure due to inadequate secretion of endogenous growth hormone (GH), short stature associated with Turner syndrome, idiopathic short stature (ISS), short stature or growth failure in short stature homeobox-containing gene (SHOX) deficiency, and short stature born small for gestational age (SGA) with no catch-up growth by 2 years to 4 years. (1.1)
- Adult: Replacement of endogenous GH in adults with GH deficiency (1.2)

2 DOSAGE AND ADMINISTRATION

- Administer by subcutaneous injection to the back of upper arm, abdomen, buttock, or thigh with regular rotation of injection sites (2.1)
- Pediatric dosage: Divide the calculated weekly dosage into equal doses given either 3, 6, or 7 days per week (2.2)
  - GH deficiency: 0.18 mg/kg/week to 0.3 mg/kg/week (2.2)
  - Turner syndrome: Up to 0.375 mg/kg/week (2.2)
  - ISS: Up to 0.37 mg/kg/week (2.2)
  - SHOX deficiency: 0.35 mg/kg/week (2.2)
  - SGA: Up to 0.47 mg/kg/week (2.2)
- Adult dosage: Either of the following two dosing regimens may be used:
  - Non-weight based dosing: Initiate with a dose of approximately 0.2 mg/day (range, 0.15 mg/day to 0.3 mg/day) and increase the dose every 1 to 2 months by increments of approximately 0.1 mg/day to 0.2 mg/day, according to individual patient requirements (2.3)
  - Weight-based dosing (Not recommended for obese patients): Initiate at 0.006 mg/kg daily and increase the dose according to individual patient requirements to a maximum of 0.0125 mg/kg daily (2.3)
- See Full Prescribing Information for reconstitution instructions (2.4)

3 DOSAGE FORMS AND STRENGTHS

For injection:

- 5 mg lyophilized powder in a single-patient-use vial (3)
- 10 mg lyophilized powder in a single-patient-use vial (3)

4 CONTRAINDICATIONS

- Acute critical illness (4,5.1)
- Pediatric patients with Prader-Willi syndrome who are severely obese, have a history of upper airway obstruction or sleep apnea, or have severe respiratory impairment due to risk of sudden death (4, 5.2)
- Active malignancy (4)
- Hypersensitivity to ZOMACTON, its excipients, or diluents (4)
- Active proliferative or severe non-proliferative diabetic retinopathy (4)
- Pediatric patients with closed epiphyses (4)

5 WARNINGS AND PRECAUTIONS

- Increased Risk of Neoplasm: Second neoplasms have occurred in childhood cancer survivors. Monitor patients with preexisting tumors for progression or recurrence. (5.3)
- Glucose Intolerance and Diabetes Mellitus: ZOMACTON may decrease insulin sensitivity, particularly at higher doses. Monitor glucose levels periodically in all patients receiving ZOMACTON, especially in patients with existing diabetes mellitus or at risk for development. (5.4)
- Intracranial Hypertension (IH): Has been reported usually within 8 weeks of initiation. Perform fundoscopic examinations prior to initiation and periodically thereafter. If papilledema occurs, stop treatment. (5.5)
- Hypersensitivity: Serious hypersensitivity reactions may occur. In the event of an allergic reaction, seek prompt medical attention. (5.6)
- Fluid Retention: May occur in adults and may be dose dependent. (5.7)
- Hypoadrenalism: Monitor patients for reduced serum cortisol levels and/or need for glucocorticoid dose increases in those with known hypoadrenalism. (5.8)
- Hypothyroidism: Monitor thyroid function periodically as hypothyroidism may occur or worsen after initiation of somatropin. (5.9)
- Slipped Capital Femoral Epiphysis in Pediatric Patients: May occur; evaluate patients with onset of a limp or hip/knee pain. (5.10)
- Progression of Preexisting Scoliosis in Pediatric Patients: Monitor patients with scoliosis for progression. (5.11)
- Pancreatitis: Has been reported; consider pancreatitis in patients with abdominal pain, especially pediatric patients. (5.12)
- Risk of Serious Adverse Reactions in Infants due to Benzyl Alcohol Preservative: Serious and fatal adverse reactions can occur in neonates and infants treated with benzyl alcohol-preserved drugs, including the diluent for ZOMACTON 5 mg. If administering ZOMACTON 5 mg to infants, reconstitute with 0.9% sodium chloride injection. (5.13)

6 ADVERSE REACTIONS

Common adverse reactions reported in adult and pediatric patients include: upper respiratory infection, fever, pharyngitis, headache, otitis media, edema, arthralgia, paresthesia, myalgia, carpal tunnel syndrome, peripheral edema, flu syndrome, hypothyroidism, hyperglycemia, and impaired glucose tolerance. (6)

To report SUSPECTED ADVERSE REACTIONS, contact Ferring Pharmaceuticals Inc. at 1-888-337-7464 or FDA at 1-800-FDA-1088 or www.fda.gov/medwatch.

7 DRUG INTERACTIONS

- Glucocorticoids: Patients treated with glucocorticoid for hypoadrenalism may require an increase in their maintenance or stress doses following initiation of ZOMACTON (7)
- Pharmacologic Glucocorticoid Therapy and Supraphysiologic Glucocorticoid Treatment: Adjust glucocorticoid replacement dosing in pediatric patients receiving glucocorticoid treatment to avoid both hypoadrenalism and an inhibitory effect on growth. (7)
- Cytochrome P450-Metabolized Drugs: ZOMACTON may alter the clearance. Monitor carefully if used with ZOMACTON (7)
- Oral Estrogen: Larger doses of ZOMACTON may be required (7)
- Insulin and/or Other Hypoglycemic Agents: Dose adjustment of insulin or hypoglycemic agent may be required (5.4, 7)

8 USE IN SPECIFIC POPULATIONS

- Pregnancy and Lactation: If ZOMACTON 5 mg is needed, reconstitute with 0.9% sodium chloride injection or use the ZOMACTON 10 mg benzyl alcohol-free formulation. (8.1, 8.2)

FULL PRESCRIBING INFORMATION

1 INDICATIONS AND USAGE

1.1 Pediatric Patients

ZOMACTON is indicated for the treatment of pediatric patients with:

- growth failure due to inadequate secretion of endogenous growth hormone (GH),
- short stature associated with Turner syndrome,
- idiopathic short stature (ISS), height standard deviation score (HSDS) ≤-2.25 and associated with growth rates unlikely to permit attainment of adult height in the normal range,
- short stature or growth failure in short stature homeobox-containing gene (SHOX) deficiency,
- short stature born small for gestational age (SGA) with no catch-up growth by 2 years to 4 years of age.

1.2 Adult Patients

ZOMACTON is indicated for the replacement of endogenous GH in adults with GH deficiency.

2 DOSAGE AND ADMINISTRATION

2.1 Administration and Use Instructions

- Therapy with ZOMACTON should be supervised by a physician who is experienced in the diagnosis and management of patients with the conditions for which ZOMACTON is indicated [see Indications and Usage (1)].
- Fundoscopic examination should be performed routinely before initiating treatment with ZOMACTON to exclude preexisting papilledema, and periodically thereafter [see Warnings and Precautions (5.5)].
- Administer ZOMACTON by subcutaneous injection to the back of the upper arm, abdomen, buttock, or thigh with regular rotation of injection sites to avoid lipoatrophy.
- ZOMACTON 5 mg and 10 mg can be administered using a standard sterile disposable syringe. For proper use, please refer to the Instructions for Use provided with the administration device. The volume of the syringe should be small enough so that the prescribed dose can be withdrawn from the vial with reasonable accuracy.

2.2 Pediatric Dosage

- Individualize dosage for each patient based on the growth response.
- Divide the calculated weekly ZOMACTON dosage into equal doses given either 3, 6, or 7 days per week.
- The recommended weekly dose in milligrams (mg) per kilogram (kg) of body weight for pediatric patients is:
  - Pediatric GH Deficiency: 0.18 mg/kg/week to 0.3 mg/kg/week (0.026 mg/kg/day to 0.043 mg/kg/day)
  - Turner syndrome: Up to 0.375 mg/kg/week (up to 0.054 mg/kg/day)
  - Idiopathic short stature: Up to 0.37 mg/kg/week (up to 0.053 mg/kg/day)
  - SHOX Deficiency: 0.35 mg/kg/week (0.05 mg/kg/day)
  - Small for Gestational Age (SGA): Up to 0.47 mg/kg/week (up to 0.067 mg/kg/day)
    - In very short pediatric patients, HSDS less than -3, and older pubertal pediatric patients consider initiating treatment with a larger dose of ZOMACTON (up to 0.067 mg/kg/day). Consider a gradual reduction in dosage if substantial catch-up growth is observed during the first few years of therapy. In pediatric patients less than 4 years of age with less severe short stature, baseline HSDS values between -2 and -3, consider initiating treatment at 0.033 mg/kg/day and titrate the dose as needed.
- Assess compliance and evaluate other causes of poor growth such as hypothyroidism, under-nutrition, advanced bone age and antibodies to recombinant human GH if patients experience failure to increase height velocity, particularly during the first year of treatment.
- Discontinue ZOMACTON for stimulation of linear growth once epiphyseal fusion has occurred [see Contraindications (4)].

2.3 Adult Dosage

- Patients who were treated with somatropin for GH deficiency in childhood and whose epiphyses are closed should be reevaluated before continuation of somatropin for GH deficient adults.
- Consider using a lower starting dose and smaller dose increment increases for geriatric patients as they may be at increased risk for adverse reactions with ZOMACTON than younger individuals [see Use in Specific Populations (8.5)].
- Estrogen-replete women and patients receiving oral estrogen may require higher doses [see Drug Interactions (7)].
- Administer the prescribed dose daily
- Either of two ZOMACTON dosing regimens may be used:
  - Non-weight based
    - Initiate ZOMACTON with a dose of approximately 0.2 mg/day (range, 0.15 mg/day to 0.3 mg/day) and increase the dose every 1 to 2 months by increments of approximately 0.1 mg/day to 0.2 mg/day, according to individual patient requirements based on the clinical response and serum insulin-like growth factor 1 (IGF-1) concentrations.
    - Decrease the dose as necessary on the basis of adverse reactions and/or serum IGF-1 concentrations above the age- and gender-specific normal range.
    - Maintenance dosages will vary considerably from person to person, and between male and female patients.
  - Weight-based
    - Initiate ZOMACTON at 0.006 mg/kg daily and increase the dose according to individual patient requirements to a maximum of 0.0125 mg/kg daily.
    - Use the patient's clinical response, adverse reactions, and determination of age- and gender-adjusted serum IGF-1 concentrations as guidance in dose titration.
    - Not recommended for obese patients as they are more likely to experience adverse reactions with this regimen.

2.4 Reconstitution

- Reconstitute ZOMACTON 5 mg with 1 mL to 5 mL of diluent, Bacteriostatic Sodium Chloride Injection, USP with 0.9% benzyl alcohol as a preservative. Do not use diluent if the patient has a known hypersensitivity to benzyl alcohol [see Contraindications (4)] or in neonates [see Warnings and Precautions (5.13)], or pregnant or lactating women [see Use in Specific Populations (8.1,8.2)] instead reconstitute with 0.9% Sodium Chloride Injection, USP, use only one dose per vial, and discard the unused portion.
- Reconstitute ZOMACTON 10 mg with 1 mL syringe of diluent, Bacteriostatic Water for Injection, USP with 0.33% metacresol as a preservative. Do not use diluent if the patient has a known hypersensitivity to metacresol [see Contraindications (4)].
- Aim the stream of diluent against the side of the vial to prevent foaming and gently swirl the vial with a rotary motion until the contents are completely dissolved and the solution is clear. Do not shake the vial since shaking or vigorous mixing will cause the solution to be cloudy.
- Inspect visually for particulate matter and discoloration. If the resulting solution is cloudy or contains particulate matter do not use.
- Occasionally, after refrigeration, some cloudiness may occur. Allow the product to warm to room temperature. If cloudiness persists or particulate matter is noted do not use.

3 DOSAGE FORMS AND STRENGTHS

ZOMACTON is a white, lyophilized powder available as:

- For injection: 5 mg in a single-patient-use vial
- For injection: 10 mg in a single-patient-use vial

4 CONTRAINDICATIONS

ZOMACTON is contraindicated in patients with:

- Acute critical illness after open heart surgery, abdominal surgery or multiple accidental trauma, or those with acute respiratory failure due to the risk of increased mortality with use of pharmacologic doses of somatropin [see Warnings and Precautions (5.1)].
- Pediatric patients with Prader-Willi syndrome who are severely obese, have a history of upper airway obstruction or sleep apnea, or have severe respiratory impairment due to the risk of sudden death [see Warnings and Precautions (5.2)].
- Active malignancy [see Warnings and Precautions (5.3)].
- Known hypersensitivity to somatropin or to any excipients of ZOMACTON. Systemic hypersensitivity reactions, including anaphylaxis and angioedema, have been reported with postmarketing use of somatropins [see Dosage and Administrations (2.4), Warnings and Precautions (5.6)].
- Active proliferative or severe non-proliferative diabetic retinopathy.
- Pediatric patients with closed epiphyses.

5 WARNINGS AND PRECAUTIONS

5.1 Increased Mortality in Patients with Acute Critical Illness

Increased mortality in patients with acute critical illness due to complications following open heart surgery, abdominal surgery or multiple accidental trauma, or those with acute respiratory failure has been reported after treatment with pharmacologic doses of somatropin [see Contraindications (4)]. Two placebo-controlled clinical trials in non-GH deficient adult patients (n=522) with these conditions in intensive care units revealed a significant increase in mortality (42% vs. 19%) among somatropin-treated patients (doses 5.3 mg/day-8 mg/day) compared to those receiving placebo. The safety of continuing ZOMACTON treatment in patients receiving replacement doses for approved indications who concurrently develop these illnesses has not been established. ZOMACTON is not indicated for the treatment of non-GH deficient adults.

5.2 Sudden Death in Pediatric Patients with Prader-Willi Syndrome

There have been reports of sudden death after initiating therapy with somatropin in pediatric patients with Prader-Willi syndrome who had one or more of the following risk factors: severe obesity, history of upper airway obstruction or sleep apnea, or unidentified respiratory infection. Male patients with one or more of these factors may be at greater risk than females. Patients with Prader-Willi syndrome should be evaluated for signs of upper airway obstruction and sleep apnea before initiation of treatment with somatropin. If, during treatment with somatropin, patients show signs of upper airway obstruction (including onset of, or increased, snoring) and/or new onset sleep apnea, treatment should be interrupted. All patients with Prader-Willi syndrome treated with somatropin should also have effective weight control and be monitored for signs of respiratory infection, which should be diagnosed as early as possible and treated aggressively [see Contraindications (4)]. ZOMACTON is not indicated for the treatment of pediatric patients who have growth failure due to Prader-Willi syndrome.

5.3 Increased Risk of Neoplasms

Active Malignancy

There is an increased risk of malignancy progression with somatropin treatment in patients with active malignancy [see Contraindications (4)]. Any preexisting malignancy should be inactive and its treatment complete prior to instituting therapy with ZOMACTON. Discontinue ZOMACTON if there is evidence of recurrent activity.

Risk of Second Neoplasm in Pediatric Patients

There is an increased risk of a second neoplasm in pediatric cancer survivors who were treated with radiation to the brain/head and who developed subsequent GH deficiency and were treated with somatropin. Intracranial tumors, in particular meningiomas, were the most common of these second neoplasms. In adults, it is unknown whether there is any relationship between somatropin replacement therapy and CNS tumor recurrence. Monitor all patients receiving ZOMACTON who have a history of GH deficiency secondary to an intracranial neoplasm for progression or recurrence of the tumor.

New Malignancy During Treatment

Because pediatric patients with certain rare genetic causes of short stature have an increased risk of developing malignancies, thoroughly consider the risks and benefits of starting ZOMACTON in these patients. If ZOMACTON is initiated, these patients should be carefully monitored for development of neoplasms.

Monitor all patients receiving ZOMACTON carefully for increased growth, or potential malignant changes, of preexisting nevi. Advise patients/caregivers to report marked changes in behavior, onset of headaches, vision disturbances and/or changes in skin pigmentation or changes in the appearance of pre-existing nevi.

5.4 Glucose Intolerance and Diabetes Mellitus

Treatment with somatropin may decrease insulin sensitivity, particularly at higher doses. New onset type 2 diabetes mellitus has been reported in patients taking somatropin. Previously undiagnosed impaired glucose tolerance and overt diabetes mellitus may be unmasked. Monitor glucose levels periodically in all patients receiving ZOMACTON, especially in those with risk factors for diabetes mellitus, such as obesity, Turner syndrome, or a family history of diabetes mellitus. Patients with preexisting type 1 or type 2 diabetes mellitus or impaired glucose tolerance should be monitored closely. The doses of antidiabetic agents may require adjustment when ZOMACTON is initiated.

5.5 Intracranial Hypertension

Intracranial hypertension (IH) with papilledema, visual changes, headache, nausea, and/or vomiting has been reported in a small number of patients treated with somatropin. Symptoms usually occurred within the first eight (8) weeks after the initiation of somatropin. In all reported cases, IH-associated signs and symptoms resolved rapidly after cessation of therapy or a reduction of the somatropin dose. Fundoscopic examination should be performed routinely before initiating treatment with ZOMACTON to exclude preexisting papilledema, and periodically thereafter. If papilledema is observed by fundoscopy, treatment should be stopped. If somatropin-induced IH is diagnosed, treatment with ZOMACTON can be restarted at a lower dose after IH-associated signs and symptoms have resolved. Patients with Turner syndrome may be at increased risk for the development of IH.

5.6 Severe Hypersensitivity

Serious systemic hypersensitivity reactions including anaphylactic reactions and angioedema have been reported with postmarketing use of somatropins. Patients and caregivers should be informed that such reactions are possible and that prompt medical attention should be sought if an allergic reaction occurs [see Contraindications (4)].

5.7 Fluid Retention

Fluid retention during somatropin replacement therapy in adults may frequently occur. Clinical manifestations of fluid retention (e.g. edema, arthralgia, myalgia, nerve compression syndromes including carpal tunnel syndrome/paresthesias) are usually transient and dose dependent.

5.8 Hypoadrenalism

Patients receiving somatropin therapy who have or are at risk for pituitary hormone deficiency(s) may be at risk for reduced serum cortisol levels and/or unmasking of central (secondary) hypoadrenalism. In addition, patients treated with glucocorticoid replacement for previously diagnosed hypoadrenalism may require an increase in their maintenance or stress doses following initiation of ZOMACTON. Monitor patients for reduced serum cortisol levels and/or need for glucocorticoid dose increases in those with known hypoadrenalism [see Drug Interactions (7)].

5.9 Hypothyroidism

Undiagnosed or untreated hypothyroidism may prevent response to ZOMACTON, in particular, the growth response in pediatric patients. Patients with Turner syndrome have an increased risk of developing autoimmune thyroid disease and primary hypothyroidism. In patients with GH deficiency, central (secondary) hypothyroidism may first become evident or worsen during somatropin treatment. Therefore, patients should have periodic thyroid function tests performed, and thyroid hormone replacement therapy should be initiated or appropriately adjusted when indicated.

5.10 Slipped Capital Femoral Epiphysis in Pediatric Patients

Slipped capital femoral epiphysis may occur more frequently in patients undergoing rapid growth. Slipped capital femoral epiphysis may lead to osteonecrosis. Cases of slipped capital femoral epiphysis with or without osteonecrosis have been reported in pediatric patients with short stature receiving somatropin. Evaluate pediatric patients receiving ZOMACTON with the onset of a limp or complaints of hip or knee pain for slipped capital femoral epiphysis and osteonecrosis and manage accordingly.

5.11 Progression of Preexisting Scoliosis in Pediatric Patients

Somatropin increases the growth rate and progression of existing scoliosis can occur in patients who experience rapid growth. Somatropin has not been shown to increase the occurrence of scoliosis. Monitor patients with a history of scoliosis for progression of scoliosis.

5.12 Pancreatitis

Cases of pancreatitis have been reported in pediatric patients and adults receiving somatropin. The risk may be greater in pediatric patients compared with adults. Published literature indicates that girls who have Turner syndrome may be at greater risk than other pediatric patients receiving somatropin. Pancreatitis should be considered in patients who develop abdominal pain.

5.13 Risk of Serious Adverse Reactions in Infants due to Benzyl Alcohol Preserved Solution

Serious and fatal adverse reactions including "gasping syndrome" can occur in neonates and infants treated with benzyl alcohol-preserved drugs, including the bacteriostatic 0.9% sodium chloride diluent provided with ZOMACTON 5 mg. The "gasping syndrome" is characterized by central nervous system depression, metabolic acidosis, and gasping respirations.

When administering ZOMACTON 5 mg to infants, reconstitute with 0.9% sodium chloride injection, not with the diluent provided. Use only one dose per vial and discard the unused portion [see Use in Specific Populations (8.4)].

5.14 Lipoatrophy

When somatropin is administered subcutaneously at the same site over a long period of time, tissue atrophy may result. Rotate injection sites when administering ZOMACTON to reduce this risk [see Dosage and Administration (2.2)].

5.15 Laboratory Tests

Serum levels of inorganic phosphorus, alkaline phosphatase, parathyroid hormone and IGF-1 may increase after ZOMACTON treatment.

6 ADVERSE REACTIONS

The following important adverse reactions are also described elsewhere in the labeling:

- Increased mortality in patients with acute critical illness [see Warnings and Precautions (5.1)]
- Fatalities in pediatric patients with Prader-Willi syndrome [see Warnings and Precautions (5.2)]
- Neoplasms [see Warnings and Precautions (5.3)]
- Glucose intolerance and diabetes mellitus [see Warnings and Precautions (5.4)]
- Intracranial hypertension [see Warnings and Precautions (5.5)]
- Severe hypersensitivity [see Warnings and Precautions (5.6)]
- Fluid retention [see Warnings and Precautions (5.7)]
- Hypoadrenalism [see Warnings and Precautions (5.8)]
- Hypothyroidism [see Warnings and Precautions (5.9)]
- Slipped capital femoral epiphysis in pediatric patients [see Warnings and Precautions (5.10)]
- Progression of preexisting scoliosis in pediatric patients [see Warnings and Precautions (5.11)]
- Pancreatitis [see Warnings and Precautions (5.12)]
- Risk of Serious Adverse Reactions in Infants due to Benzyl Alcohol Preservative [see Warnings and Precautions (5.13)]
- Lipoatrophy [see Warnings and Precautions (5.14)]

6.1 Clinical Trials Experience

Because clinical trials are conducted under varying conditions, adverse reaction rates observed during the clinical trials performed with one somatropin formulation cannot always be directly compared to the rates observed during the clinical trials performed with a different approved somatropin formulation and may not reflect the adverse reaction rates observed in practice.

Pediatric Patients

Growth Failure due to Inadequate Secretion of Endogenous Growth Hormone

ZOMACTON was evaluated in 164 pediatric patients with short stature due to GHD in an open-label study for 24 weeks. The subjects ranged in age from 2.1 to 17.7 years with a mean of 10.8 years. One hundred twenty (73%) of the subjects were male and 44 (27%) were female. Two subjects were Asian, 12 were Black, 130 were Caucasian, and 20 were categorized as 'other'.

Table 1: Adverse Reactions ≥ 5% in Pediatric Patients with Growth Failure Due to GHD Treated with ZOMACTON through 24 Weeks
Adverse Reaction | 24 Week Exposure to ZOMACTON (n=164)
Upper respiratory infection | 32%
Fever | 16%
Pharyngitis | 12%
Headache | 11%
Otitis Media | 10%
Increased cough | 9%
Abdominal pain | 7%
Anemia | 6%
Maculopapular rash | 6%
Diarrhea | 5%
Pain | 5%
Rhinitis | 5%

All pediatric patients were carefully observed for signs or laboratory abnormalities of hypothyroidism. Fifteen patients had T4 values which occasionally fell below the central laboratory's lower limit of normal; T4 levels rose to normal when tested during the next visit for all patients except one who continued to be monitored. Six of the 15 patients received thyroxine therapy before and throughout the study period, and thyroxine dose adjustments were made during the study in 3/6 subjects.

In studies with GH deficient pediatric patients, injection site pain was reported in 1.6% of patients. A mild and transient edema, which appeared in 1.6% of patients, was observed early during the course of treatment.

Short Stature Associated with Turner Syndrome

In a randomized, concurrent-controlled, open-label study, there was an increase in the occurrence of otitis media, ear disorders and surgical procedures in patients receiving another somatropin product at a dose of 0.3 mg/kg/week, compared with untreated control patients (Table 2). A similar increase in otitis media was observed in an 18-month placebo-controlled study.

Table 2: Adverse Reactions Occurring in Patients with Turner Syndrome Treated with 0.3 mg/kg/week of Another Somatropin product During a 4.7 Year Randomized Open-Label Study
 | Untreated (n=62) | Somatropin (n=74)
Surgical procedure | 27% | 45%
Otitis media | 26% | 43%
Ear disorders | 5% | 18%

Idiopathic Short Stature

Adverse reactions from a randomized, placebo-controlled study of another somatropin product dosed at 0.22 mg/kg/week are presented in Table 3. Mean fasting serum insulin concentration increased 10% in the group treated with another somatropin product at the end of treatment relative to baseline, but remained within the normal reference range.

Table 3: Adverse Reactions Occurring in Patients with Idiopathic Short Stature Treated with Another Somatropin product during a 4.4 Year Randomized Placebo-Controlled Study
Adverse Reactions | Placebo (n=31) | Another Somatropin product (n=37)
Scoliosis | 13% | 19%
Otitis media | 7% | 16%
Hyperlipidemia | 3% | 8%
Gynecomastia | 3% | 5%
Hip pain | 0% | 3%
Arthralgia | 3% | 11%
Arthrosis | 7% | 11%
Myalgia | 13% | 24%
Hypertension | 0% | 3%

In a dose-response study with 239 patients treated for 2 years, mean fasting blood glucose, mean glycosylated hemoglobin, and the incidence of elevated fasting blood glucose concentrations were similar among dose groups. One patient developed glucose intolerance and high serum HbA1c.

Short Stature or Growth Failure in SHOX Deficiency

Adverse reactions from a 2-year open-label study with another somatropin product compared to no treatment are presented in Table 4. During the study, the proportion of patients who had at least one IGF-1 concentration greater than 2.0 SD above the age- and gender-appropriate mean was 37.0% for the somatropin-treated group vs. 0% patients for the untreated group. The proportion of patients who had at least one IGFBP-3 concentration greater than 2.0 SD above the age and gender appropriate mean was 59% for the somatropin treated group vs. 29% for the untreated group.

Table 4: Adverse Reactions Occurring in Patients with SHOX Deficiency Treated with Another Somatropin product for 2 years
 | Untreated (n=25) | Another Somatropin product (n=27)
Arthralgia | 8% | 11%
Gynecomastia | 0% | 8%
Excessive number of cutaneous nevi | 0% | 7%
Scoliosis | 0% | 4%

Small for Gestational Age (SGA) with No Catch-up Growth by 2 Years to 4 Years of Age

In a 2-year study, 193 pediatric patients were treated with another somatropin product using 2 different treatment regimens: a fixed dose of 0.067 mg/kg/day (FHD group) or an individually adjusted dose regimen (IAD group; starting dose 0.035 mg/kg/day which could be increased as early as Month 3 to 0.067 mg/kg/day based on a validated growth prediction model). Adverse reactions included common childhood infectious diseases, otitis media, headaches, and slipped capital femoral epiphysis (n=1). Six patients (4 in the FHD group and 2 in the IAD group whose dose was increased from 0.035 mg/kg/day to 0.067 mg/kg/day [one at Month 3 and one at Year 1])) had impaired fasting glucose at Year 2. Two of 6 had impaired fasting glucose during the study, and 1 discontinued treatment at month 15 as a consequence. At study completion, 20-25% of patients had serum IGF-1 SDS values > +2.

The following adverse reactions were reported from an observational study of 340 pediatric patients who received another somatropin product with an average dosage of 0.041 mg/kg/day for an average of 3 years: type 2 diabetes mellitus (n=1), carpal tunnel syndrome (n=1) and exacerbation of preexisting scoliosis (n=1).

Adult Patients

Adult-Onset GH Deficiency

In the first 6 months of controlled blinded trials during which patients received either another somatropin product or placebo, patients who received this other somatropin product experienced a statistically significant increase in edema (another somatropin product 17% vs. placebo 4%, p=0.043) and peripheral edema (12% vs. 0%, respectively, p=0.017). Edema, muscle pain, joint pain, and joint disorder were reported early in therapy and tended to be transient or responsive to dosage titration.

Two of 113 patients developed carpal tunnel syndrome after beginning maintenance therapy without a low dose (0.00625 mg/kg/day) lead-in phase. Symptoms abated in these patients after dosage reduction.

All adverse reactions with ≥5% overall occurrence rate during 12 or 18 months of replacement therapy with another somatropin product are shown in Table 5 (adult-onset patients) and in Table 6 (childhood-onset patients).

Adult patients treated with another somatropin product who had been diagnosed with GH deficiency in childhood reported adverse reactions less frequently than those with adult-onset GH deficiency.

Table 5: Adverse Reactions Occurring ≥5% in Adult-Onset Growth Hormone-Deficient Patients Treated with Another Somatropin product for 18 Months as Compared with 6-Month Placebo and 12-Month Exposure to Another Somatropin product [Abbreviations: GH= another somatropin product; n=number of patients receiving treatment in the period stated]
 | 18 Months Exposure
Adverse Reaction | [Placebo (6 Months)/GH (12 Months)] | 18 Months GH Exposure
 | (n=46) | (n=52)
Edema [p=0.04 as compared to placebo (6 months).] | 15% | 21%
Arthralgia | 15% | 17%
Paresthesia | 13% | 17%
Myalgia | 13% | 14%
Pain | 13% | 14%
Rhinitis | 11% | 14%
Peripheral edema [p=0.02 as compared to placebo (6 months).] | 17% | 12%
Back pain | 11% | 10%
Headache | 11% | 8%
Hypertension | 4% | 8%
Acne | 0% | 6%
Joint disorder | 2% | 6%
Surgical procedure | 2% | 6%
Flu syndrome | 7% | 4%

Childhood-Onset GH Deficiency

Two double-blind, placebo-controlled trials were conducted in 67 adult patients who had received previous somatropin treatment during childhood. Patients were randomized to receive either placebo injections or another somatropin product (0.00625 mg/kg/day for the first 4 weeks, then 0.0125 mg/kg/day thereafter) for the first 6 months, followed by open-label use of another somatropin product for the next 12 months for all patients. The patients in these studies reported side effects less frequently than those with adult-onset GH deficiency. During the placebo-controlled phase (first 6 months) of the study, elevations of serum glutamic oxaloacetic transferase were reported significantly more often for somatropin-treated (12.5%) than placebo-treated patients (0.0%, p=0.031). No other events were reported significantly more often for somatropin-treated patients during the placebo-controlled phase.

Table 6: Adverse Reactions Occurring ≥5% in Childhood-Onset Growth Hormone-Deficient Patients Treated with Another Somatropin product for 18 Months as Compared with 6-Month Placebo and 12-Month Exposure to Another Somatropin product [Abbreviations: GH=another somatropin product; n=number of patients receiving treatment in the period stated; ALT=alanine aminotransferase, formerly SGPT; AST=aspartate aminotransferase, formerly SGOT.]
 | 18 Months Exposure | 18 Months GH Exposure
Adverse Reaction | [Placebo (6 Months)/GH (12 Months)] | 18 Months GH Exposure
 | (n=35) | (n=32)
Flu syndrome | 23% | 16%
AST increased [p=0.03 as compared to placebo (6 months).] | 6% | 13%
Headache | 11% | 9%
Asthenia | 3% | 6%
Cough increased | 0% | 6%
Edema | 9% | 6%
Hypesthesia | 0% | 6%
Myalgia | 6% | 6%
Pain | 9% | 6%
Rhinitis | 6% | 6%
ALT increased | 6% | 6%
Respiratory disorder | 6% | 3%
Gastritis | 6% | 0%
Pharyngitis | 14% | 3%

In an ongoing post-marketing observational study of treatment with another somatropin product in 3,102 GH-deficient adults, hypertension, dyspnea, and sleep apnea were reported by 1% to less than 10% of patients after various durations of treatment.

6.2 Postmarketing Experience

The following adverse reactions have been identified during post approval use of somatropin or ZOMACTON. Because the following adverse events are reported voluntarily from a population of uncertain size, it is not always possible to reliably estimate their frequency or establish a causal relationship to drug exposure.

Gastrointestinal disorders— Pancreatitis

Immune system disorders — Serious systemic hypersensitivity reactions including anaphylactic reactions and angioedema

Metabolism and nutrition disorders — New-onset type 2 diabetes mellitus

Musculoskeletal and connective tissue disorders – osteonecrosis in pediatric patients

Neoplasms benign, malignant and unspecified — Leukemia has been reported in a small number of GH deficient pediatric patients treated with somatropin, somatrem (methionylated rhGH), and GH of pituitary origin

Nervous system disorders — Headaches (common in pediatric patients and occasional in adults)

Reproductive system and breast disorders — Gynecomastia

Skin and subcutaneous tissue disorders — Increase in size or number of cutaneous nevi

7 DRUG INTERACTIONS

Table 7 includes a list of drugs with clinically important drug interactions when administered concomitantly with ZOMACTON and instructions for preventing or managing them.

Table 7: Clinically Important Drug Interactions with ZOMACTON

Glucocorticoids
Clinical Impact: | Microsomal enzyme 11β-hydroxysteroid dehydrogenase type 1 (11βHSD-1) is required for conversion of cortisone to its active metabolite, cortisol, in hepatic and adipose tissue. ZOMACTON inhibits 11βHSD-1. Consequently, individuals with untreated GH deficiency have relative increases in 11βHSD-1 and serum cortisol. Initiation of ZOMACTON may result in inhibition of 11βHSD-1 and reduced serum cortisol concentrations.
Intervention: | Patients treated with glucocorticoid replacement for hypoadrenalism may require an increase in their maintenance or stress doses following initiation of ZOMACTON[seeWarnings and Precautions (5.8)].
Examples: | Cortisone acetate and prednisone may be affected more than others since conversion of these drugs to their biologically active metabolites is dependent on the activity of 11βHSD-1.
Pharmacologic Glucocorticoid Therapy and Supraphysiologic Glucocorticoid Treatment
Clinical Impact: | Pharmacologic glucocorticoid therapy and supraphysiologic glucocorticoid treatment may attenuate the growth promoting effects of ZOMACTON in pediatric patients.
Intervention: | Carefully adjust glucocorticoid replacement dosing in pediatric patients receiving glucocorticoid treatments to avoid both hypoadrenalism and an inhibitory effect on growth.
Cytochrome P450-Metabolized Drugs
Clinical Impact: | Limited published data indicate that somatropin treatment increases cytochrome P450 (CP450)-mediated antipyrine clearance. ZOMACTON may alter the clearance of compounds known to be metabolized by CP450 liver enzymes.
Intervention: | Careful monitoring is advisable when ZOMACTON is administered in combination with drugs metabolized by CP450 liver enzymes.
Oral Estrogen
Clinical Impact: | Oral estrogens may reduce the serum IGF-1 response to ZOMACTON.
Intervention: | Patients receiving oral estrogen replacement may require greater ZOMACTON dosages[seeDosage and Administration (2.2)].
Insulin and/or Other Hypoglycemic Agents
Clinical Impact: | Treatment with ZOMACTON may decrease insulin sensitivity, particularly at higher doses.
Intervention: | Patients with diabetes mellitus may require adjustment of their doses of insulin and/or other hypoglycemic agents[seeWarnings and Precautions (5.4)].

8 USE IN SPECIFIC POPULATIONS

8.1 Pregnancy

Risk Summary

The ZOMACTON 5 mg diluent contains benzyl alcohol. Because benzyl alcohol is rapidly metabolized by a pregnant woman, benzyl alcohol exposure in the fetus is unlikely. However, adverse reactions have occurred in premature neonates and low birth weight infants who received intravenously administered benzyl alcohol-containing drugs [see Warnings and Precautions (5.13) and Use in Specific Populations (8.4)]. Therefore, if ZOMACTON 5mg is needed during pregnancy, reconstitute with 0.9% sodium chloride injection, use only one dose per vial, and discard the unused portion, or use a ZOMACTON 10 mg benzyl alcohol-free formulation.

Limited published data do not report an association with somatropin and major birth defects, miscarriage, or adverse maternal or fetal outcomes when somatropin is used in pregnancy. Published reports indicate that somatropin does not cross the placenta. Animal reproduction studies have not been conducted with ZOMACTON.

The estimated background risk of major birth defects and miscarriage for the indicated population is unknown. All pregnancies have a background risk of birth defect, loss, or other adverse outcomes. In the U.S. general population, the estimated background risk of major birth defects and miscarriage in clinically recognized pregnancies is 2-4% and 15-20%, respectively.

8.2 Lactation

Risk Summary

The ZOMACTON 5mg diluent contains benzyl alcohol. Because benzyl alcohol is rapidly metabolized by a lactating woman, benzyl alcohol exposure in the breastfed infant is unlikely. However, adverse reactions have occurred in premature neonates and low birth weight infants who received intravenously administered benzyl alcohol-containing drugs [see Warnings and Precautions (5.13) and Use in Specific Populations (8.4)]. If ZOMACTON 5mg is needed during lactation, reconstitute with 0.9% sodium chloride injection, use only one dose per vial, and discard after use or use a ZOMACTON 10 mg benzyl alcohol-free formulation.

There is no information regarding the presence of somatropin in human milk. Limited published data indicate that exogenous somatropin does not increase normal breastmilk concentrations of growth hormone. No adverse effects on the breastfed infant have been reported with somatropin. The developmental and health benefits of breastfeeding should be considered along with the mother's clinical need for ZOMACTON and any potential adverse effects on the breastfed child from ZOMACTON or from the underlying maternal condition.

8.4 Pediatric Use

Safety and effectiveness of ZOMACTON in pediatric patients have been established in growth failure due to inadequate secretion of endogenous growth hormone, short stature associated with Turner syndrome, idiopathic short stature (ISS), short stature or growth failure in SHOX deficiency, and short stature in children born small for gestational age (SGA) with no catch-up growth by 2 years to 4 years of age.

Growth Failure due to Inadequate Secretion of Endogenous Growth Hormone

Safety and effectiveness of ZOMACTON have been established in pediatric patients with growth failure due to growth hormone deficiency based on data from a multi-center, open-label study in 164 pediatric patients conducted for a two-year period [see Clinical Studies (14.1)].

Short Stature associated with Turner Syndrome

Safety and effectiveness of ZOMACTON have been established in pediatric patients with short stature associated with Turner syndrome based on data from one long-term, randomized, open-label, Canadian multicenter, concurrently controlled study; two long-term, open-label multicenter, historically controlled US studies; and one long-term, randomized, US dose-response study with another somatropin product in 181 pediatric patients [see Clinical Studies (14.2)].

Idiopathic Short Stature (ISS)

Safety and effectiveness of ZOMACTON have been established in pediatric patients with ISS based on data from two randomized, multicenter studies, one placebo-controlled study and one dose-response study with another somatropin product in 310 pediatric patients [see Clinical Studies (14.3)].

Short Stature or Growth Failure in SHOX Deficiency

Safety and effectiveness of ZOMACTON have been established in pediatric patients with short stature or growth failure in SHOX deficiency based on data from a randomized, controlled, two-year, three-arm, open-label study with another somatropin product in 52 pediatric patients [see Clinical Studies (14.4)].

Short Stature in Children Born Small for Gestational Age (SGA) with No Catch-up Growth by Age 2 Years to 4 Years of Age

Safety and effectiveness of ZOMACTON have been established in pediatric patients with short stature born SGA with no catch-up growth based on data from two clinical studies with another somatropin product in 228 pediatric patients [see Clinical Studies (14.5)].

Toxicity (Gasping Syndrome) with Benzyl Alcohol-Preserved Solution

Serious adverse reactions including fatal reactions and the "gasping syndrome" occurred in premature neonates and infants in the intensive care unit who received drugs containing benzyl alcohol as a preservative. In these cases, benzyl alcohol dosages of 99 mg/kg/day to 234 mg/kg/day produced high levels of benzyl alcohol and its metabolites in the blood and urine (blood levels of benzyl alcohol were 0.61 mmol/L to 1.378 mmol/L). The maximal daily uptake of benzyl alcohol is 39 mg at ZOMACTON doses of 0.067 mg/kg/day.

Additional adverse reactions included gradual neurological deterioration, seizures, intracranial hemorrhage, hematologic abnormalities, skin breakdown, hepatic and renal failure, hypotension, bradycardia, and cardiovascular collapse. Preterm, low-birth weight infants may be more likely to develop these reactions because they may be less able to metabolize benzyl alcohol. When administering ZOMACTON 5 mg to infants, reconstitute with 0.9% sodium chloride injection, not with the diluent provided. Use only one dose per vial and discard the unused portion [see Warnings and Precautions (5.13)].

8.5 Geriatric Use

The safety and effectiveness of somatropin in patients aged 65 years and over has not been evaluated in clinical studies. Elderly patients may be more sensitive to the action of somatropin, and therefore may be more prone to development of adverse reactions. A lower starting dose and smaller dose increments should be considered for geriatric patients [see Dosage and Administration (2.3)].

9 DRUG ABUSE AND DEPENDENCE

9.1 Controlled Substance

ZOMACTON contains somatropin, which is not a controlled substance.

9.2 Abuse

Inappropriate use of somatropin may result in significant negative health consequences.

9.3 Dependence

Somatropin is not associated with drug related withdrawal adverse reactions.

10 OVERDOSAGE

Acute overdosage may lead initially to hypoglycemia and subsequently to hyperglycemia. Overdose with somatropin is likely to cause fluid retention. Long-term overdosage may result in signs and symptoms of gigantism or acromegaly consistent with the known effects of excess growth hormone.

11 DESCRIPTION

Somatropin is a human growth hormone (GH) produced by recombinant DNA technology using Escherichia coli. The protein is comprised of 191 amino acid residues and has a molecular weight of about 22,124 daltons. The amino acid sequence is identical to that of human growth hormone of pituitary origin.

ZOMACTON (somatropin) for injection is a sterile, white lyophilized powder, intended for subcutaneous injection after reconstitution with the accompanying diluent.

ZOMACTON 5 mg single-patient-use vial contains 5 mg of somatropin and mannitol (30 mg). Each 5 mg vial is co-packaged with a 5 mL vial of diluent containing Bacteriostatic Sodium Chloride Injection, USP, with 0.9% benzyl alcohol as a preservative, and Water for Injection, USP.

ZOMACTON 10 mg single-patient-use vial contains 10 mg of somatropin, mannitol (10 mg), dibasic sodium phosphate (1.415 mg), and monobasic sodium phosphate (0.608 mg). Each 10 mg vial is co-packaged with a 1 mL syringe of diluent containing Bacteriostatic Water for Injection, USP with 0.33% metacresol as a preservative.

Reconstituted solutions have a pH in the range of 7 to 9.

12 CLINICAL PHARMACOLOGY

12.1 Mechanism of Action

Somatropin binds to dimeric GH receptors located within the cell membranes of target tissue cells. This interaction results in intracellular signal transduction and subsequent induction of transcription and translation of GH-dependent proteins including IGF-1, IGF BP-3 and acid-labile subunit. Somatropin has direct tissue and metabolic effects or effects mediated indirectly by IGF-1, including stimulation of chondrocyte differentiation, and proliferation, stimulation of hepatic glucose output, protein synthesis, and lipolysis.

Somatropin stimulates skeletal growth in pediatric patients with GHD as a result of effects on the growth plates (epiphyses) of long bones. The stimulation of skeletal growth increases linear growth rate (height velocity) in most somatropin-treated pediatric patients. Linear growth is facilitated in part by increased cellular protein synthesis.

12.2 Pharmacodynamics

Subcutaneous administration of a single dose of 4 mg ZOMACTON in healthy subjects (n=54) with suppressed endogenous growth hormone results in an increased mean (SD) IGF-1 level from 233 (95) ng/mL predose to maximal level of 414 (120) ng/mL after approx. 24 hours. After 96 hours, the subjects displayed a mean (SD) IGF-1 concentration of 228 (74) ng/mL, comparable to the predose value.

12.3 Pharmacokinetics

Absorption — Somatropin has been studied following subcutaneous, and intravenous administration in adult healthy subjects. A single subcutaneous dose of 4 mg ZOMACTON in healthy subjects (n=54) with suppressed endogenous growth hormone resulted in a mean (SD) Cmax of 38.1 (19.3) ng/mL after approximately 4.5 hours. The absolute bioavailability of somatropin is approximately 70% after subcutaneous administration.

Distribution — The mean (SD) apparent volume of distribution of somatropin after single dose subcutaneous administration of 4 mg ZOMACTON in healthy subjects is 53.3 (24.6) L.

Elimination

Metabolism — Extensive metabolism studies have not been conducted. The metabolic fate of somatropin involves classical protein catabolism in both the liver and kidneys.

Excretion - In healthy subjects, mean somatropin clearance is 0.133 L/min following intravenous administration. The mean elimination half-life of intravenous somatropin is 0.42 hours, whereas subcutaneously administered somatropin has a mean half-life of 2.3 hours. The longer half-life observed after subcutaneous administration is due to slow absorption from the injection site. Urinary excretion of intact somatropin has not been measured.

Specific Populations

Geriatric patients — The pharmacokinetics of somatropin have not been studied in patients greater than 65 years of age.

Pediatric patients — The pharmacokinetics of somatropin in pediatric patients are similar to those of adults.

Male and Female Patients — No gender-specific pharmacokinetic studies have been performed with somatropin. The available literature indicates that the pharmacokinetics of somatropin are similar in men and women.

Patients with Renal or Hepatic Impairment — No studies have been performed with somatropin.

12.6 Immunogenicity

The observed incidence of anti-drug antibodies is highly dependent on the sensitivity and specificity of the assay. Differences in assay methods preclude meaningful comparisons of the incidence of anti-drug antibodies in the studies described below with the incidence of anti-drug antibodies in other studies, including those of ZOMACTON or other somatropins.

In a clinical trial with another recombinant growth hormone during the first 6 months of somatropin therapy in 314 naive patients, 1.6% developed specific antibodies to somatropin (binding capacity ≥0.02 mg/L). None had antibody concentrations which exceeded 2 mg/L. Throughout 8 years of this same study, two patients (0.6%) had binding capacity >2 mg/L. Neither patient demonstrated a decrease in growth velocity at or near the time of increased antibody production. It has been reported that growth attenuation from pituitary-derived GH may occur when antibody concentrations are >1.5 mg/L.

13 NONCLINICAL TOXICOLOGY

13.1 Carcinogenesis, Mutagenesis, Impairment of Fertility

ZOMACTON has shown no potential for mutagenicity in the Ames Test. Carcinogenesis and fertility studies have not been conducted with ZOMACTON.

14 CLINICAL STUDIES

14.1 Pediatric Patients with Growth Failure Due to Inadequate Secretion of Endogenous Growth Hormone

A 2-year open-label, multi-center study with ZOMACTON was conducted in the United States and in Israel in 164 pediatric patients with short stature due to GHD. The subjects ranged in age from 2.1 to 17.7 years with a mean of 10.8 years. One hundred twenty (73%) of the subjects were male and 44 (27%) were female. Two subjects were Asian, 12 were Black, 130 were Caucasian, and 20 were categorized as 'other'.

The primary efficacy of the product was assessed by calculating height velocity. Mean cumulative increases in height velocity from baseline of 6.6, 4.6, and 6.3 cm/year were attained by 24 weeks of treatment (p < 0.01) in Naïve Type I (serum GH < 10 ng/mL in response to at least two provocative pharmacological tests), Naïve Type II (integrated GH level < 3.5 ng/mL with or without at least one serum GH ≥ 10 ng/mL), and Non-Naïve (treated with GH up to study Day 1, or previously treated and discontinued GH treatment at least 6 months prior to study Day 1) subjects, respectively. After 12 months of treatment, the mean cumulative increases in height velocity from baseline were 5.7, 4.4 and 5.3 cm/year (p= 0.01) in Naïve Type I, Naïve Type II, and Non-Naïve subjects, respectively.

14.2 Pediatric Patients with Short Stature Associated with Turner Syndrome

One long-term, randomized, open-label, Canadian multicenter, concurrently controlled study; two long-term, open-label multicenter, historically controlled US studies; and one long-term, randomized, US dose-response study were conducted to evaluate the efficacy of another somatropin product for treatment of short stature due to Turner syndrome.

The Canadian randomized study compared near-adult height outcomes for patients treated with another somatropin product to those of a concurrent control group who received no injections. Patients received a dosage of 0.3 mg/kg/week given in divided doses 6 times per week from a mean age of 12 years for a mean duration of 5 years. Puberty was induced with a standardized estrogen regimen initiated at 13 years of age for both treatment groups.

In two of the US studies, the effect of long-term treatment with another somatropin product (0.375 mg/kg/week given in divided doses either 3 times per week or daily) on adult height was determined by comparing adult heights in the treated patients with those of age-matched historical controls with Turner syndrome who received no growth-promoting therapy. Puberty was induced with a standardized estrogen regimen initiated after 14 years of age in one study; in the second study patients treated early (before 11 years of age) were randomized to begin pubertal induction at either age 12 (n=26) or 15 (n=29) years (conjugated estrogens, 0.3 mg escalating to 0.625 mg daily); those whose treatment was initiated after 11 years of age began estrogen replacement after 1 year of treatment with another somatropin product.

In a dose-response study in the US, patients were treated from a mean age of 11 years for a mean duration of 5 years with a weekly dosage of either 0.27 mg/kg or 0.36 mg/kg of another somatropin product administered in divided doses 3 or 6 times weekly.

In summary, patients with Turner syndrome (total n=181 from the 4 studies above) treated to adult height achieved statistically significant average height gains ranging from 5.0 to 8.3 cm (see Table 8).

Table 8: Height Gain Results [Data shown are mean values.] of Studies with Another Somatropin product in Patients with Turner Syndrome
Study | Group | Study Design [RCT: randomized controlled trial; MHT: matched historical controlled trial; RDT: randomized dose-response trial.] | Another Somatropin product Treated Number at Adult Height | GH Age (yr) | Estrogen Age (yr) | GH Duration (yr) | Adult Height Gain (cm) [Analysis of covariance vs. controls.]
Canadian |  | RCT | 27 | 11.7 | 13 | 4.7 | 5.4
US 1 |  | MHT | 17 | 9.1 | 15.2 | 7.6 | 7.4
US 2 | A [GH age <11 yr, estrogen age 15 yr.] | MHT | 29 | 9.4 | 15 | 6.1 | 8.3
US 2 | B [GH age <11 yr, estrogen age 12 yr.] |  | 26 | 9.6 | 12.3 | 5.6 | 5.9
US 2 | C [GH age >11 yr, estrogen at month 12.] |  | 51 | 12.7 | 13.7 | 3.8 | 5
US 3 |  | RDT | 31 | 11.1 | 8-13.5 | 5.3 | ~5 [Compared with historical data.]

14.3 Pediatric Patients with Idiopathic Short Stature

Two randomized, multicenter studies, 1 placebo-controlled and 1 dose-response, were conducted with another somatropin product in pediatric patients with idiopathic short stature. The diagnosis of idiopathic short stature was made after excluding other known causes of short stature, as well as GH deficiency. The placebo-controlled study enrolled 71 pediatric patients (55 males, 16 females) 9 to 15 years old (mean age 12 ± 1.5 years), with short stature, 68 of whom received another somatropin product. Patients were predominately prepubertal (Tanner I, 45%) or in early puberty (Tanner II, 47%) at baseline. In this double-blind study, patients received subcutaneous injections of either another somatropin product 0.222 mg/kg/week, or placebo given in divided doses 3 times per week until height velocity decreased to ≤1.5 cm/year ("final height"). Final height measurements were available for 33 subjects (22 treated, 11 placebo) after a mean treatment duration of 4.4 years (range 0.1-9.1 years).

Results are presented in Table 9. The number of patients whose final height was above the 5th percentile of the general population height standard for age and sex was significantly greater in the treated group than the placebo group (41% vs. 0%), as was the number of patients who gained at least 1 SDS unit in height across the duration of the study (50% vs. 0%).

Table 9: Baseline Height Characteristics and Effect of Another Somatropin product on Final Height in Placebo-Controlled Study [Abbreviations: BPH=baseline predicted height; CI=confidence interval; FH=final height; NA=not applicable; SDS=standard deviation score.] , [For final height population.]
 | Placebo (n=11) Mean (SD) | Another Somatropin product (n=22) Mean (SD) | Treatment Effect Mean (95% CI) | p-value
Baseline height SDS | -2.75 (0.6) | -2.7 (0.6) | NA | 0.77
BPH SDS | -2.3 (0.8) | -2.1 (0.7) | NA | 0.53
Final height SDS [Between-group comparison was performed using analysis of covariance with baseline predicted height SDS as the covariate. Treatment effect is expressed as least squares mean (95% CI).] | -2.3 (0.6) | -1.8 (0.8) | 0.51 (0.10, 0.92) | 0.017
FH SDS – baseline height SDS | 0.4 (0.2) | 0.9 (0.7) | 0.51 (0.04, 0.97) | 0.034
FH SDS – BPH SDS | -0.1 (0.6) | 0.3 (0.6) | 0.46 (0.02, 0.89) | 0.043

The dose-response study included 239 pediatric patients (158 males, 81 females), 5 to 15 years old, (mean age 10 ± 2 years). Mean ± SD baseline characteristics included: height SDS -3.21 ± 0.70, predicted adult height SDS -2.63 ± 1.08, and height velocity

SDS -1.09 ± 1.15. All but 3 patients were prepubertal. Patients were randomized to one of three treatment groups:

0.24 mg/kg/week; 0.24 mg/kg/week for 1 year, followed by 0.37 mg/kg/week; and 0.37 mg/kg/week. Height velocity was assessed by dose during the first 2 years of therapy. After completing the initial 2-year dose-response phase of the study, 50 patients were followed to final height.

Patients who received the dosage of 0.37 mg/kg/week had a significantly greater increase in mean height velocity after 2 years of treatment than patients who received 0.24 mg/kg/week (4.04 vs. 3.27 cm/year, p=0.003). The results are presented in Table 10. While no patient had height above the 5th percentile in any dosage group at baseline, 82% of the patients who received 0.37 mg/kg/week and 47% of the patients who received 0.24 mg/kg/week achieved final heights above the 5th percentile of the general population height standards (p=NS).

Table 10: Idiopathic Short Stature Study Results: Final Height Minus Baseline Predicted Height [Abbreviations: FH=final height; PH=predicted height; CI=confidence interval; cm=centimeters.]
 | Placebo-controlled Trial 3× per week dosing |  | Dose Response Trial 6× per week dosing
 | Placebo | Another Somatropin product | Another Somatropin product | Another Somatropin product | Another Somatropin product
 | (n=10) | 0.22 mg/kg (n=22) | 0.24 mg/kg (n=13) | 0.24/0.37 mg/kg (n=13) | 0.37 mg/kg (n=13)
FH – Baseline PH Mean (95% CI), cm | -0.7 (-3.6, 2.3) | +2.2 (0.4, 3.9) | +5.4 (2.8, 7.9) | +6.7 (4.1, 9.2) | +7.2 (4.6, 9.8)

14.4 Pediatric Patients with Short Stature or Growth Failure with SHOX Deficiency

A randomized, controlled, two-year, three-arm, open-label study was conducted to evaluate the efficacy of another somatropin product for treatment of short stature in pediatric patients with SHOX deficiency who were not GH–deficient. A total of 52 patients (24 male, 28 female) with SHOX deficiency, 3 to 12 years of age, were randomized to either a treated arm (27 patients; mean age 7 ± 2 years) or an untreated control arm (25 patients; mean age 8 ± 3 years). To determine the comparability of treatment effect between patients with SHOX deficiency and patients with Turner syndrome, the third study arm enrolled 26 patients with Turner syndrome, 5 to 12 years of age (mean age 8 ± 2 years), to treatment. All patients were prepubertal at study entry. Patients in the treated group(s) received daily subcutaneous injections of 0.05 mg/kg of another somatropin product, equivalent to 0.35 mg/kg/week. Patients in the untreated group received no injections. The results are presented in Table 11.

Table 11: Summary of Results in Patients with SHOX deficiency and Turner Syndrome
 | SHOX Deficiency |  |  | Turner Syndrome
 | Untreated (n=24) Mean (SD) | Another Somatropin product (n=27) Mean (SD) | Treatment Difference [Positive values favor somatropin] Mean (95% CI) | Another Somatropin product (n=26) Mean (SD)
Height Velocity (cm/yr)
1st Year | 5.2 (1.1) | 8.7 (1.6) [Statistically significantly different from untreated, p<0.001.] | +3.5 (2.8, 4.2) | 8.9 (2.0)
2nd Year | 5.4 (1.2) | 7.3 (1.1) | +2.0 (1.3, 2.6) | 7.0 (1.1)
Height Gain (cm)
Baseline to 1st Year | +5.4 (1.2) | +9.1 (1.5) | +3.7 (2.9, 4.5) | +8.9 (1.9)
Baseline to 2nd Year | +10.5 (1.9) | +16.4 (2.0) | +5.8 (4.6, 7.1) | +15.7 (2.7)
Height SDS Gain
Baseline to 1st Year | +0.1 (0.5) | +0.7 (0.5) | +0.5 (0.3, 0.8) | +0.8 (0.5)
Baseline to 2nd Year | +0.2 (0.5) | +1.2 (0.7) | +1.0 (0.7, 1.3) | +1.2 (0.2)
Patients with height SDS > -2.0 at 2 years | 1 (4%) | 11 (41%) [Statistically significantly different from untreated, p<0.05.] | -- | 8 (31%)

14.5 Pediatric Patients Born Small for Gestational Age (SGA) Who Fail to Demonstrate Catch-up Growth by 2 Years to 4 Years of Age

A 2-year, open-label, multicenter, European study enrolled 193 prepubertal, non-GH deficient children with mean chronological age 7 ± 2 years (range: 3 to 12). Study entry criteria included birth weight <10th percentile and/or birth length SDS <-2 for gestational age, and height SDS for chronological age ≤-3. Exclusion criteria included syndromal conditions (e.g., Turner syndrome), chronic disease (e.g., diabetes mellitus), and tumor activity. The primary objective was to demonstrate that the increase from baseline in height SDS after 1 year of treatment with another somatropin product would be similar when treatment is administered according to an individually adjusted dose (IAD) regimen or a fixed high dose (FHD) regimen. The height increases would be considered similar if the lower bound of the 95% confidence interval (CI) for the mean difference between the groups (IAD – FHD) was greater than -0.5 height SDS. Pediatric patients were randomized to either a FHD (0.067 mg/kg/day; n=99) or an IAD treatment group (n=94). The initial dosage in the IAD treatment group was 0.035 mg/kg/day. The dosage was increased to 0.067 mg/kg/day in those patients in the IAD group whose 1-year height gain predicted at Month 3 was <0.75 height SDS (n=40) or whose actual height gain measured at Year 1 was <0.75 height SDS (n=11). Approximately 85% of the randomized patients completed 2 years of therapy.

The results are presented in Table 12. The results were similar when children who entered puberty during the study were removed from the analysis.

Table 12: Results for Height SDS and Change from Baseline in Height SDS at Year 1 and Year 2 After Treatment with Another Somatropin product of Short Children Born SGA Who Fail to Demonstrate Catch-up Growth [Abbreviations: IAD=individually adjusted dose; FHD=fixed high dose; SD=standard deviation; SDS=standard deviation score]
 | IAD Group 0.035 to 0.067 mg/kg/day Mean (SD) | FHD Group 0.067 mg/kg/day Mean (SD) | Between-Group Difference IAD - FHD [Least squares mean difference ± standard error and 95% confidence interval based on ANCOVA model with treatment and gender as fixed effects, and baseline height SDS, baseline chronological age, baseline bone age, and mid-parental target height SDS as covariates.]
Baseline | (n=86) | (n=93) | -0.0 ± 0.1
 | -3.9 (0.6) | -3.9 (0.7) | (-0.2, 0.2)
 |  |  | p-value = 0.95
Year 1 | (n=86) [Only children with actual height measurements were included in the Year 1 and Year 2 analyses.] | (n=93) | -0.3 ± 0.1
Height SDS | -3.0 (0.7) | -2.7 (0.7) | (-0.4, -0.2)
Change from baseline | 0.9 (0.4) | 1.1 (0.4) | p-value <0.001
Year 2 | (n=82) | (n=88) | -0.3 ± 0.1
Height SDS | -2.5 (0.8) | -2.2 (0.7) | (-0.4, -0.1)
Change from baseline | 1.4 (0.5) | 1.6 (0.5) | p-value = 0.003

An open-label, multicenter, single arm study conducted in France, during which 35 prepubertal, non-GH deficient children were treated for 2 years with another somatropin product 0.067 mg/kg/day. Mean chronological age at baseline was 9 ± 0.9 years (range: 7 to 11). Additional study entry criteria included birth length SDS <-2 or <3rd percentile for gestational age, and height SDS for chronological age <-2. Exclusion criteria included syndromal conditions (e.g., Turner syndrome), chronic disease (e.g., diabetes mellitus), and any active disease. All 35 patients completed the study. Mean height SDS increased from a baseline value of -2.7 (SD 0.5) to -1.5 (SD 0.6) after 2 years of treatment.

14.6 Adult Patients with Growth Hormone Deficiency

Two studies in patients with adult-onset GH deficiency (total n=98) and two studies in adult patients with childhood-onset GH deficiency (total n=67) were designed to assess the effects of replacement therapy with another somatropin product. Adult-onset patients and childhood-onset patients differed by diagnosis (organic vs. idiopathic pituitary disease), body size (average vs. small [mean height and weight]), and age (mean 44 vs. 29 years). These four studies each included a 6-month randomized, blinded, placebo-controlled phase, during which approximately half of the patients received placebo injections, while the other half received injections with another somatropin product. The 6-month, double-blind phase was followed by 12 months of open-label somatropin treatment for all patients. The dosages of this other somatropin product for all studies were identical: 1 month of treatment at 0.00625 mg/kg/day followed by 0.0125 mg/kg/day for the next 5 months. The primary efficacy measures were body composition (lean body mass and fat mass) and lipid parameters. Lean body mass was determined by bioelectrical impedance analysis (BIA), validated with potassium 40. Body fat was assessed by BIA and sum of skinfold thickness. Lipid subfractions were analyzed by standard assay methods in a central laboratory.

In patients with adult-onset GH deficiency, treatment with another somatropin product (vs. placebo) resulted in an increase in mean lean body mass (2.59 vs. -0.22 kg, p<0.001) and a decrease in body fat (-3.27 vs. 0.56 kg, p<0.001). Similar changes were seen in childhood-onset GH deficient patients. Changes in lean body mass persisted throughout the 18-month period for both the adult-onset and childhood-onset groups; the changes in fat mass persisted in the childhood-onset group. Serum concentrations of high-density lipoprotein (HDL) cholesterol which were low at baseline (mean, 30.1 mg/mL and 33.9 mg/mL in adult-onset and childhood-onset patients, respectively) had normalized by the end of 18 months of treatment with this other somatropin product (mean change of 13.7 mg/dL and 11.1 mg/dL for the adult-onset and childhood-onset groups, respectively p<0.001).

16 HOW SUPPLIED/STORAGE AND HANDLING

16.1 How Supplied

ZOMACTON (somatropin) for injection is a white, lyophilized powder available as:

NDC | ZOMACTON | Diluent | Additional Items
NDC 55566-1801-1 | 5 mg single-patient-use vial | 5 mL vial of diluent, Bacteriostatic Sodium Chloride Injection, USP with 0.9% benzyl alcohol
NDC 55566-1901-1 | 10 mg single-patient-use vial | 1 mL syringe of diluent, Bacteriostatic Water for Injection, USP with 0.33% metacresol | 25G reconstitution needle

16.2 Storage and Handling

Before Reconstitution

Store ZOMACTON vials refrigerated at 36° to 46°F (2° to 8°C) in the original carton to protect from light. Avoid freezing the accompanying diluent.

After Reconstitution

If needed, store ZOMACTON 5 mg vials that have been reconstituted with co-packaged Bacteriostatic Sodium Chloride Injection, USP (with 0.9% benzyl alcohol) refrigerated at 36° to 46°F (2° to 8°C) for up to 14 days. Do not freeze.

If needed, store ZOMACTON 10 mg vials that have been reconstituted with co-packaged Bacteriostatic Water for Injection, USP (with 0.33% metacresol) refrigerated at 36° to 46°F (2° to 8°C) for up to 28 days. Do not freeze.

17 PATIENT COUNSELING INFORMATION

Advise the patient to read the FDA-approved patient labeling (Instructions for Use).

- Neoplasms – Advise childhood cancer survivors/caregivers that individuals treated with brain/head radiation are at increased risk of secondary neoplasms and as a precaution need to be monitored for recurrence. Advise patients/caregivers to report marked changes in behavior, onset of headaches, vision disturbances and/or changes in skin pigmentation or changes in the appearance of pre-existing nevi.
- Fluid Retention - Advise patients that fluid retention during ZOMACTON replacement therapy in adults may frequently occur. Inform patients of the clinical manifestations of fluid retention (e.g. edema, arthralgia, myalgia, nerve compression syndromes including carpal tunnel syndrome/paresthesias) and to report to their healthcare provider any of these signs or symptoms occur during treatment with ZOMACTON.
- Pancreatitis - Advise patients/caregivers that pancreatitis may develop and to report to their healthcare provider any new onset abdominal pain.
- Hypoadrenalism - Advise patients/caregivers who have or who are at risk for pituitary hormone deficiency(s) that hypoadrenalism may develop and to report to their healthcare provider if they experience hyperpigmentation, extreme fatigue, dizziness, weakness, or weight loss.
- Hypothyroidism - Advise patients/caregivers that undiagnosed/untreated hypothyroidism may prevent an optimal response to ZOMACTON. Advise patients/caregivers they may require periodic thyroid function tests.
- Intracranial Hypertension - Advise patients/caregivers to report to their healthcare provider any visual changes, headache, and nausea and/or vomiting.
- Hypersensitivity Reactions – Advise patients/caregivers that serious systemic hypersensitivity reactions (anaphylaxis and angioedema) are possible and that prompt medical attention should be sought if an allergic reaction occurs.
- Glucose Intolerance/ Diabetes Mellitus – Advise patients/caregivers that new onset impaired glucose intolerance/diabetes mellitus or exacerbation of preexisting diabetes mellitus can occur and monitoring of blood glucose during treatment with ZOMACTON may be needed.
- Females of Reproductive Potential – Instruct patients to inform their healthcare provider if they are pregnant or planning to become pregnant as they may potentially require the use of a different formulation of ZOMACTON.

Manufactured by:

FERRING PHARMACEUTICALS INC.
PARSIPPANY, NJ 07054

U.S. License No. 2112

XXXXXXXXXX

Instructions for Use

ZOMACTON®
(zoh-MACK-ton)
[somatropin]
for Injection

Read the Instructions for Use that come with your ZOMACTON® before you start using it and each time you get a refill. There may be new information. This leaflet does not take the place of talking to your healthcare provider about your medical condition or treatment. Before you use ZOMACTON for the first time, make sure your healthcare provider shows you the right way to use it.

Supplies needed for your ZOMACTON Injection

- ZOMACTON 5mg (See Figure A) containing:
  - 1 vial of ZOMACTON 5mg growth hormone in a powder
  - 1 vial of liquid (diluent) containing Bacteriostatic Sodium Chloride Injection, USP (with 0.9% benzyl alcohol as a preservative) (5mL). This is used to mix your ZOMACTON 5mg.

Figure A

or

- ZOMACTON 10mg (See Figure B) containing:
  - 1 vial of ZOMACTON 10mg growth hormone in a powder
  - 1 syringe of liquid (diluent) containing Bacteriostatic Water for Injection, USP (with 0.33% Metacresol as a preservative) (1 mL). This is used to mix your ZOMACTON 10mg.
  - 25 gauge mixing needle

Figure B

The following additional supplies (See Figure C) will be needed:

- Syringe and needle for injection. Your healthcare provider will tell you the size of the syringe and needle to use.
- Alcohol swab
- Puncture-resistant container (See Step 4: Disposing of used syringes, needles, and vials)

Figure C

Preparing for Your ZOMACTON Injection

- Place the supplies you will need on a clean, flat surface in a well-lit area.
- Wash your hands thoroughly with soap and water.

Important: The liquids are different for the 5 mg and 10 mg vials.

- Do not use the 5 mg liquid with the 10 mg ZOMACTON.
- Do not use the 10 mg liquid with the 5 mg ZOMACTON.

Preparing ZOMACTON 5mg Liquid for Injection:

- Remove the hard plastic cap from the top of the liquid vial by gently pushing up on the edge of the cap (See Figure D). Do not remove the rubber stopper.

Figure D

- Use an alcohol swab to wipe off the top of the liquid vial (See Figure E). After cleaning, do not touch the rubber stopper.

Figure E

- Remove the needle cap from the syringe while making sure you do not touch the needle (See Figure F). Do not throw away the needle cap.

Figure F

- Hold the barrel of the syringe with 1 hand and pull back on the plunger with the other hand until you have drawn up the amount of air that is the same as the amount of liquid your healthcare provider has prescribed (See Figure G).

Figure G

- Insert the needle into the liquid vial through the center of the clean rubber stopper. Push down on the plunger until all the air is released into the vial (See Figure H).

Figure H

- Hold the vial with 1 hand and carefully turn the vial upside down, making sure the syringe needle stays in the vial. The tip of the needle should be below the surface of the liquid.
- With your other hand, gently pull back the plunger until the amount of liquid your healthcare provider prescribed is in the syringe (See Figure I).

Figure I

When the syringe is correctly filled with the liquid, remove the syringe and needle from the vial and recap the needle.

Preparing ZOMACTON 10mg Liquid for Injection:

- Remove the syringe tip cap from the top of the pre-filled liquid syringe and attach the 25G mixing needle that comes with your ZOMACTON (See Figure J).

Figure J

Diluting Your ZOMACTON

- Only use the liquid that comes with the 5 mg ZOMACTON to mix the 5 mg growth hormone. Only use the liquid that comes with the 10 mg ZOMACTON to mix the 10 mg growth hormone.
- Remove the hard plastic cap of the growth hormone vial (See Figure K).

Figure K

- Clean the top of the growth hormone vial with an alcohol swab (See Figure L).

Figure L

- Remove the needle cap from the syringe filled with liquid and insert the needle into the center of the rubber stopper on the growth hormone vial (See Figure M).

Figure M

- Point the needle toward the side of the vial and slowly push the plunger so that the liquid squirts onto the side of the vial and not directly onto the powder.
- When all the liquid is in the growth hormone vial, remove the needle from the vial (See Figure N).

Figure N

- Recap the needle and throw away the syringe.

Mixing ZOMACTON

- Hold the vial between your hands and gently roll it until the mixture is clear. Do not shake the vial. Your ZOMACTON is ready for injection.
- Sometimes the vial may need to sit a few seconds before the mixture becomes clear. Do not use the mixture in the vial if it remains cloudy or you see particles floating in the mixture. If air bubbles appear, let the growth hormone sit for a while until they disappear.
- Write the date you mixed the growth hormone on the vial label. The 5 mg vial must be used within 14 days. The 10 mg vial must be used within 28 days.
- Store your mixed growth hormone and all unopened vials of growth hormone in the refrigerator at 36°F to 46°F (2°C to 8°C). Do not freeze.

Step 1: Preparing the Injection

You are now ready for your ZOMACTON injection.

- Wash your hands thoroughly with soap and water.
- Check that the vial of growth hormone you are using is clear and that the date of mixing is within 14 days if you are using ZOMACTON 5 mg or 28 days if you are using ZOMACTON 10 mg.
- Clean the top of the growth hormone vial with an alcohol swab. Do not touch the rubber stopper after cleaning (See Figure O).

Figure O

- Remove the needle cap from the syringe and insert the needle into the center of the rubber stopper on the growth hormone vial (See Figure P).

Figure P

- Gently pull back the plunger until the amount of growth hormone solution your healthcare provider has prescribed is in the syringe (See Figure Q).

Figure Q

- Remove the needle from the vial when the syringe is correctly filled with the solution (See Figure R). Recap the needle.

Figure R

Step 2: Choosing an Injection Site

- There are different sites you can use for your injections. These sites should be rotated (See Figure S).

Figure S

If you notice any of the following signs, contact your healthcare provider:

- A lump, bruise or redness at the injection site that does not go away.
- Any sign of infection at the injection site (pus, redness, heat or persistent pain).
- Severe, sharp pain or ache at injection site that does not go away.
- Rash at the injection site.

Step 3: Injecting ZOMACTON

Using a circular motion, clean the injection site with an alcohol swab, starting at the injection site and moving outward about 2 inches. Let the skin air dry.

- Check that the correct dose is in the syringe.
- Remove the needle cap. Hold the syringe like a pencil in 1 hand.
- With your free hand, pinch the skin around the site with the thumb and forefinger of the other hand (See Figure T). Quickly insert the needle into the skin at a 45° - 90° angle with a quick, dart-like motion.

Figure T

- Holding the syringe in place, pull back a little on the plunger and check to see if any blood flows into the syringe (See Figure U). If you see blood in the syringe, it means that you have entered a blood vessel. Do not inject ZOMACTON. Withdraw the needle. Throw away the syringe and needle in a puncture-resistant container. Do not use the same syringe or any of the other supplies that you used for this injection. Repeat the steps to prepare a new syringe for injection. Choose and clean a new injection site.

Figure U

- If no blood appears in the syringe, slowly push down plunger all the way until the syringe is completely empty (See Figure V).

Figure V

- Quickly remove the needle from the skin and apply pressure to the injection site with a dry sterile gauze pad or cotton ball. A drop of blood may appear. Apply a small bandage if needed. Throw away the needle and syringe in your puncture-resistant disposal container.
- Do not share your syringes, needles, or vials with anyone else. You may give them or get an infection from them.

Step 4: Disposing of used syringes, needles, and vials

- To prevent needle-stick injury and spread of infection, do not try to re-cap the needle.
- Place used needles, syringes, and vials in a closeable, puncture-resistant container. You may use a sharps container (such as a red biohazard container), hard plastic container (such as a detergent bottle), or metal container (such as an empty coffee can). Do not use glass or clear plastic containers. Ask your healthcare provider for instructions on the right way to throw away (dispose of) the container. There may be state and local laws about how you should throw away used needles and syringes.
- If you do not have a FDA-cleared sharps disposal container, you may use a household container that is:
  - made of a heavy-duty plastic,
  - can be closed with a tight-fitting, puncture-resistant lid, without sharps being able to come out,
  - upright and stable during use,
  - leak-resistant, and
  - properly labeled to warn of hazardous waste inside the container.

- When your sharps disposal container is almost full, you will need to follow your community guidelines for the right way to dispose of your sharps disposal container. There may be state or local laws about how you should throw away used needles and syringes. For more information about safe sharps disposal, and for specific information about sharps disposal in the state that you live in, go to the FDA's website at: http://www.fda.gov/safesharpsdisposal
- Do not throw used needles, syringes, or vials in your household trash or recycle.
- Keep the disposal container, needles, syringes, and vials of ZOMACTON out of reach of children.

This Instructions for Use has been approved by the Food and Drug Administration.

MANUFACTURED BY:

FERRING PHARMACEUTICALS INC.
PARSIPPANY, NJ 07054

U.S. License No. 2112

XXXXXXXXXX
Rev.7/2025

PRINCIPAL DISPLAY PANEL - 5 mg Kit Carton

NDC 55566-1801-1

FERRING
PHARMACEUTICALS

ZOMACTON®
(somatropin) for Injection

5 mg per vial

For subcutaneous use only

1 single-patient-use vial

Reconstitute with Bacteriostatic Sodium Chloride Injection,
USP containing 0.9% benzyl alcohol. Gently swirl. Do not shake.

Storage before and after reconstitution: Refrigerate at 2°C
to 8°C (36°C to 46°F). Do not freeze. Protect from light.
After reconstitution: Use within 14 days.

Rx only

PRINCIPAL DISPLAY PANEL - 10 mg Kit Carton - 1901

NDC 55566-1901-1

FERRING
PHARMACEUTICALS

ZOMACTON®
(somatropin) for Injection

10 mg per vial

For subcutaneous use only

1 single-patient-use vial

Reconstitute with Bacteriostatic Water for injection, USP containing 0.33% metacresol.
Gently swirl. Do not shake.

Storage before and after reconstitution: Refrigerate at 2°C to 8°C (36°F to 46°F).
Do not freeze. Protect from light. After reconstitution: Use within 28 days.

Rx only